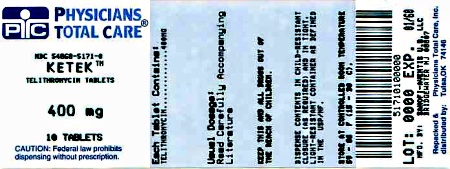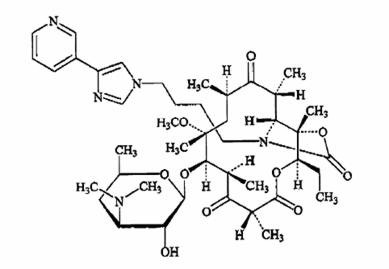 DRUG LABEL: Ketek
NDC: 54868-5171 | Form: TABLET, FILM COATED
Manufacturer: Physicians Total Care, Inc.
Category: prescription | Type: HUMAN PRESCRIPTION DRUG LABEL
Date: 20120502

ACTIVE INGREDIENTS: telithromycin 400 mg/1 1
INACTIVE INGREDIENTS: croscarmellose sodium; hypromelloses; magnesium stearate; cellulose, microcrystalline; polyethylene glycol; povidone; ferric oxide red; talc; titanium dioxide; ferric oxide yellow

KETEK®
(telithromycin) Tablets

BOXED WARNING

Ketek is contraindicated in patients with myasthenia gravis. There have been reports of fatal and life-threatening respiratory failure in patients with myasthenia gravis associated with the use of Ketek. (See CONTRAINDICATIONS.)

To reduce the development of drug-resistant bacteria and maintain the effectiveness of KETEK and other antibacterial drugs, KETEK should be used only to treat infections that are proven or strongly suspected to be caused by bacteria.

DESCRIPTION

KETEK® tablets contain telithromycin, a semisynthetic antibacterial in the ketolide class for oral administration. Chemically, telithromycin is designated as Erythromycin, 3-de[(2,6-dideoxy-3-C-methyl-3-O-methyl-α-L-ribo-hexopyranosyl)oxy]-11,12-dideoxy-6-O-methyl-3-oxo-12,11-[oxycarbonyl[[4-[4-(3-pyridinyl)-1H-imidazol-1-yl]butyl]imino]]-.

Telithromycin, a ketolide, differs chemically from the macrolide group of antibacterials by the lack of α-L-cladinose at position 3 of the erythronolide A ring, resulting in a 3-keto function. It is further characterized by a C11-12 carbamate substituted by an imidazolyl and pyridyl ring through a butyl chain. Its empirical formula is C43H65N5O10 and its molecular weight is 812.03. Telithromycin is a white to off-white crystalline powder. The following represents the chemical structure of telithromycin.

KETEK tablets are available as light-orange, oval, film-coated tablets, each containing 400 mg or 300 mg of telithromycin, and the following inactive ingredients: croscarmellose sodium, hypromellose, magnesium stearate, microcrystalline cellulose, polyethylene glycol, povidone, red ferric oxide, talc, titanium dioxide, and yellow ferric oxide.

CLINICAL PHARMACOLOGY

Pharmacokinetics

Absorption

Following oral administration, telithromycin reached maximal concentration at about 1 hour (0.5 – 4 hours).

It has an absolute bioavailability of 57% in both young and elderly subjects.

The rate and extent of absorption are unaffected by food intake, thus KETEK tablets can be given without regard to food.

In healthy adult subjects, peak plasma telithromycin concentrations of approximately 2 µg/mL are attained at a median of 1 hour after an 800-mg oral dose.

Steady-state plasma concentrations are reached within 2 to 3 days of once daily dosing with telithromycin 800 mg.

Following oral dosing, the mean terminal elimination half-life of telithromycin is 10 hours.

The pharmacokinetics of telithromycin after administration of single and multiple (7 days) once daily 800-mg doses to healthy adult subjects are shown in Table 1.

Table 1
 | Mean (SD)
Parameter | Single dose (n=18) | Multiple dose (n=18)
Cmax (µg/mL) | 1.9 (0.80) | 2.27 (0.71)
Tmax (h) [Median (min–max) values] | 1.0 (0.5–4.0) | 1.0 (0.5–3.0)
AUC(0–24) (µg∙h/mL) | 8.25 (2.6) | 12.5 (5.4)
Terminal t1/2 (h) | 7.16 (1.3) | 9.81 (1.9)
C24h (µg/mL) | 0.03 (0.013) | 0.07 (0.051)
SD=Standard deviation
Cmax=Maximum plasma concentration
Tmax=Time to Cmax
AUC=Area under concentration vs. time curve
t1/2=Terminal plasma half-life
C24h=Plasma concentration at 24 hours post-dose

In a patient population, mean peak and trough plasma concentrations were 2.9 µg/mL (±1.55), (n=219) and 0.2 µg/mL (±0.22), (n=204), respectively, after 3 to 5 days of KETEK 800 mg once daily.

Distribution

Total in vitro protein binding is approximately 60% to 70% and is primarily due to human serum albumin.

Protein binding is not modified in elderly subjects and in patients with hepatic impairment.

The volume of distribution of telithromycin after intravenous infusion is 2.9 L/kg.

Telithromycin concentrations in bronchial mucosa, epithelial lining fluid, and alveolar macrophages after 800 mg once daily dosing for 5 days in patients are displayed in Table 2.

Table 2
 | Hours post-dose | Mean concentration (µg/mL) |  | Tissue/Plasma Ratio
 | Hours post-dose | Tissue or fluid | Plasma | Tissue/Plasma Ratio
Bronchial mucosa | 2 | 3.88 [Units in mg/kg] | 1.86 | 2.11
 | 12 | 1.41 | 0.23 | 6.33
 | 24 | 0.78 | 0.08 | 12.11
Epithelial lining fluid | 2 | 14.89 | 1.86 | 8.57
 | 12 | 3.27 | 0.23 | 13.8
 | 24 | 0.84 | 0.08 | 14.41
Alveolar macrophages | 2 | 65 | 1.07 | 55
 | 8 | 100 | 0.605 | 180
 | 24 | 41 | 0.073 | 540

Telithromycin concentration in white blood cells exceeds the concentration in plasma and is eliminated more slowly from white blood cells than from plasma. Mean white blood cell concentrations of telithromycin peaked at 72.1 µg/mL at 6 hours, and remained at 14.1 µg/mL 24 hours after 5 days of repeated dosing of 600 mg once daily. After 10 days, repeated dosing of 600 mg once daily, white blood cell concentrations remained at 8.9 µg/mL 48 hours after the last dose.

Metabolism

In total, metabolism accounts for approximately 70% of the dose. In plasma, the main circulating compound after administration of an 800-mg radio-labeled dose was parent compound, representing 56.7% of the total radioactivity. The main metabolite represented 12.6% of the AUC of telithromycin. Three other plasma metabolites were quantified, each representing 3% or less of the AUC of telithromycin.

It is estimated that approximately 50% of its metabolism is mediated by CYP 450 3A4 and the remaining 50% is CYP 450-independent.

Elimination

The systemically available telithromycin is eliminated by multiple pathways as follows: 7% of the dose is excreted unchanged in feces by biliary and/or intestinal secretion; 13% of the dose is excreted unchanged in urine by renal excretion; and 37% of the dose is metabolized by the liver.

Special populations

Gender

There was no significant difference between males and females in mean AUC, Cmax, and elimination half-life in two studies; one in 18 healthy young volunteers (18 to 40 years of age) and the other in 14 healthy elderly volunteers (65 to 92 years of age), given single and multiple once daily doses of 800 mg of KETEK.

Hepatic insufficiency

In a single-dose study (800 mg) in 12 patients and a multiple-dose study (800 mg) in 13 patients with mild to severe hepatic insufficiency (Child Pugh Class A, B and C), the Cmax, AUC and t1/2 of telithromycin were similar to those obtained in age- and sex-matched healthy subjects. In both studies, an increase in renal elimination was observed in hepatically impaired patients indicating that this pathway may compensate for some of the decrease in metabolic clearance. No dosage adjustment is recommended due to hepatic impairment.

(See PRECAUTIONS, General and DOSAGE AND ADMINISTRATION)

Renal insufficiency

In a multiple-dose study, 36 subjects with varying degrees of renal impairment received 400 mg, 600 mg, or 800 mg KETEK once daily for 5 days. There was a 1.4-fold increase in Cmax,ss, and a 1.9-fold increase in AUC (0–24)ss at 800 mg multiple doses in the severely renally impaired group (CLCR < 30 mL/min) compared to healthy volunteers. Renal excretion may serve as a compensatory elimination pathway for telithromycin in situations where metabolic clearance is impaired. Patients with severe renal impairment are prone to conditions that may impair their metabolic clearance. Therefore, in the presence of severe renal impairment (CLCR < 30 mL/min), a reduced dosage of KETEK is recommended. (See DOSAGE AND ADMINISTRATION)

In a single-dose study in patients with end-stage renal failure on hemodialysis (n=10), the mean Cmax and AUC values were similar to normal healthy subjects when KETEK was administered 2 hours post-dialysis. However, the effect of dialysis on removing telithromycin from the body has not been studied.

Multiple insufficiency

The effects of co-administration of ketoconazole in 12 subjects (age ≥ 60 years), with impaired renal function were studied (CLCR= 24 to 80 mL/min). In this study, when severe renal insufficiency (CLCR < 30 mL/min, n=2) and concomitant impairment of CYP 3A4 metabolism pathway were present, telithromycin exposure (AUC (0–24)) was increased by approximately 4- to 5-fold compared with the exposure in healthy subjects with normal renal function receiving telithromycin alone. In the presence of severe renal impairment (CLCR < 30 mL/min), with coexisting hepatic impairment, a reduced dosage of KETEK is recommended. (See PRECAUTIONS, General and DOSAGE AND ADMINISTRATION)

Geriatric

Pharmacokinetic data show that there is an increase of 1.4-fold in exposure (AUC) in 20 patients ≥ 65 years of age with community acquired pneumonia in a Phase III study, and a 2.0-fold increase in exposure (AUC) in 14 subjects ≥ 65 years of age as compared with subjects less than 65 years of age in a Phase I study. No dosage adjustment is required based on age alone.

Drug-drug interactions

In vitro interactions

In vitro studies using a model compound have shown that telithromycin may act as an inhibitor for the hepatic uptake transporters OATP1B1 and OATP1B3. Although the clinical relevance of this finding is unknown, it is possible that concomitant administration of telithromycin with drugs that are substrates of OATP family members could result in increased plasma concentrations of the co-administered drug.

In vivo interactions

Studies were performed to evaluate the effect of CYP 3A4 inhibitors on telithromycin and the effect of telithromycin on drugs that are substrates of CYP 3A4 and CYP 2D6. In addition, drug interaction studies were conducted with several other concomitantly prescribed drugs.

CYP 3A4 inhibitors

Itraconazole

A multiple-dose interaction study with itraconazole showed that Cmax of telithromycin was increased by 22% and AUC by 54%.

Ketoconazole

A multiple-dose interaction study with ketoconazole showed that Cmax of telithromycin was increased by 51% and AUC by 95%.

Grapefruit juice

When telithromycin was given with 240 mL of grapefruit juice after an overnight fast to healthy subjects, the pharmacokinetics of telithromycin were not affected.

CYP 3A4 substrates

Cisapride

Steady-state peak plasma concentrations of cisapride (an agent with the potential to increase QT interval) were increased by 95% when co-administered with repeated doses of telithromycin, resulting in significant increases in QTc. (See CONTRAINDICATIONS)

Simvastatin

When simvastatin was co-administered with telithromycin, there was a 5.3-fold increase in simvastatin Cmax, an 8.9-fold increase in simvastatin AUC, a 15-fold increase in the simvastatin active metabolite Cmax, and a 12-fold increase in the simvastatin active metabolite AUC. (See PRECAUTIONS)

In another study, when simvastatin and telithromycin were administered 12 hours apart, there was a 3.4-fold increase in simvastatin Cmax, a 4.0-fold increase in simvastatin AUC, a 3.2-fold increase in the active metabolite Cmax, and a 4.3-fold increase in the active metabolite AUC. (See PRECAUTIONS)

Midazolam

Concomitant administration of telithromycin with intravenous or oral midazolam resulted in 2- and 6-fold increases, respectively, in the AUC of midazolam due to inhibition of CYP 3A4-dependent metabolism of midazolam. (See PRECAUTIONS)

CYP 2D6 substrates

Paroxetine

There was no pharmacokinetic effect on paroxetine when telithromycin was co-administered.

Metoprolol

When metoprolol was co-administered with telithromycin, there was an increase of approximately 38% on the Cmax and AUC of metoprolol, however, there was no effect on the elimination half-life of metoprolol. Telithromycin exposure is not modified with concomitant single-dose administration of metoprolol. (See PRECAUTIONS, Drug interactions)

Other drug interactions

Digoxin

The plasma peak and trough levels of digoxin were increased by 73% and 21%, respectively, in healthy volunteers when co-administered with telithromycin. However, trough plasma concentrations of digoxin (when equilibrium between plasma and tissue concentrations has been achieved) ranged from 0.74 to 2.17 ng/mL. There were no significant changes in ECG parameters and no signs of digoxin toxicity. (See PRECAUTIONS)

Theophylline

When theophylline was co-administered with repeated doses of telithromycin, there was an increase of approximately 16% and 17% on the steady-state Cmax and AUC of theophylline. Co-administration of theophylline may worsen gastrointestinal side effects such as nausea and vomiting, especially in female patients. It is recommended that telithromycin should be taken with theophylline 1 hour apart to decrease the likelihood of gastrointestinal side effects.

Sotalol

Telithromycin has been shown to decrease the Cmax and AUC of sotalol by 34% and 20%, respectively, due to decreased absorption.

Warfarin

When co-administered with telithromycin in healthy subjects, there were no pharmacodynamic or pharmacokinetic effects on racemic warfarin.

Oral contraceptives

When oral contraceptives containing ethinyl estradiol and levonorgestrel were co-administered with telithromycin, the steady-state AUC of ethinyl estradiol did not change and the steady-state AUC of levonorgestrel was increased by 50%. The pharmacokinetic/pharmacodynamic study showed that telithromycin did not interfere with the antiovulatory effect of oral contraceptives containing ethinyl estradiol and levonorgestrel.

Ranitidine, antacid

There was no clinically relevant pharmacokinetic interaction of ranitidine or antacids containing aluminum and magnesium hydroxide on telithromycin.

Rifampin

During concomitant administration of rifampin and KETEK in repeated doses, Cmax and AUC of telithromycin were decreased by 79%, and 86%, respectively. (See PRECAUTIONS, Drug Interactions)

Microbiology

Telithromycin belongs to the ketolide class of antibacterials and is structurally related to the macrolide family of antibiotics. Telithromycin concentrates in phagocytes where it exhibits activity against intracellular respiratory pathogens. In vitro, telithromycin has been shown to demonstrate concentration-dependent bactericidal activity against isolates of Streptococcus pneumoniae (including multi-drug resistant isolates [MDRSP [MDRSP=Multi-drug resistant Streptococcus pneumoniae includes isolates known as PRSP (penicillin-resistant Streptococcus pneumoniae), and are isolates resistant to two or more of the following antimicrobials: penicillin, 2nd generation cephalosporins (e.g., cefuroxime), macrolides, tetracyclines, and trimethoprim/sulfamethoxazole.] ]).

Mechanism of action

Telithromycin blocks protein synthesis by binding to domains II and V of 23S rRNA of the 50S ribosomal subunit. By binding at domain II, telithromycin retains activity against gram-positive cocci (e.g., Streptococcus pneumoniae) in the presence of resistance mediated by methylases (erm genes) that alter the domain V binding site of telithromycin. Telithromycin may also inhibit the assembly of nascent ribosomal units.

Mechanism of resistance

Staphylococcus aureus and Streptococcus pyogenes with the constitutive macrolide-lincosamide-streptogramin B (cMLSB) phenotype are resistant to telithromycin.

Mutants of Streptococcus pneumoniae derived in the laboratory by serial passage in subinhibitory concentrations of telithromycin have demonstrated resistance based on L22 riboprotein mutations (telithromycin MICs are elevated but still within the susceptible range), one of two reported mutations affecting the L4 riboprotein, and production of K-peptide. The clinical significance of these laboratory mutants is not known.

Cross resistance

Telithromycin does not induce resistance through methylase gene expression in erythromycin-inducibly resistant bacteria, a function of its 3-keto moiety. Telithromycin has not been shown to induce resistance to itself.

List of Microorganisms

Telithromycin has been shown to be active against most strains of the following microorganisms, both in vitro and in clinical settings as described in the INDICATIONS AND USAGE section.

Aerobic gram-positive microorganisms

Streptococcus pneumoniae (including multi-drug resistant isolates [MDRSP [MDRSP=Multi-drug resistant Streptococcus pneumoniae includes isolates known as PRSP (penicillin-resistant S. pneumoniae), and are isolates resistant to two or more of the following antimicrobials: penicillin, 2nd generation cephalosporins (e.g., cefuroxime), macrolides, tetracyclines, and trimethoprim/sulfamethoxazole.] ])

Aerobic gram-negative microorganisms

Haemophilus influenzae

Moraxella catarrhalis

Other microorganisms

Chlamydophila (Chlamydia) pneumoniae

Mycoplasma pneumoniae

The following in vitro data are available, but their clinical significance is unknown.

At least 90% of the following microorganisms exhibit in vitro minimum inhibitory concentrations (MICs) less than or equal to the susceptible breakpoint for telithromycin. However, the safety and efficacy of telithromycin in treating clinical infections due to these microorganisms have not been established in adequate and well-controlled clinical trials.

Aerobic gram-positive microorganisms

Staphylococcus aureus (methicillin and erythromycin susceptible isolates only)

Streptococcus pyogenes (erythromycin susceptible isolates only)

Streptococci (Lancefield groups C and G)

Other microorganisms

Legionella pneumophila

Susceptibility Test Methods

When available, the clinical microbiology laboratory should provide cumulative results of in vitro susceptibility test results for antimicrobial drugs used in local hospitals and practice areas to the physician as periodic reports that describe the susceptibility profile of nosocomial and community-acquired pathogens. These reports should aid the physician in selecting the most effective antimicrobial.

Dilution techniques

Quantitative methods are used to determine antimicrobial minimum inhibitory concentrations (MICs). These MICs provide estimates of the susceptibility of bacteria to antibacterial compounds. The MICs should be determined using a standardized procedure. Standardized procedures are based on dilution methods (broth or agar dilution)^1,3 or equivalent with standardized inoculum and concentrations of telithromycin powder. The MIC values should be interpreted according to criteria provided in Table 3.

Diffusion techniques

Quantitative methods that require measurement of zone diameters also provide reproducible estimates of the susceptibility of bacteria to antibiotics. One such standardized procedure^2,3 requires the use of standardized inoculum concentrations. This procedure uses paper disks impregnated with 15 µg telithromycin to test the susceptibility of microorganisms to telithromycin. Disc diffusion zone sizes should be interpreted according to criteria in Table 3.

Table 3. Susceptibility Test Result Interpretive Criteria for Telithromycin
 | Minimal Inhibitory Concentrations (µg/mL) |  |  | Disk Diffusion (zone diameters in mm)
Pathogen | S | I | R | S | I | R
Streptococcus pneumoniae | ≤ 1 | 2 | ≥ 4 | ≥ 19 | 16–18 | ≤ 15
Haemophilus influenzae | ≤ 4 | 8 | ≥ 16 | ≥ 15 | 12–14 | ≤ 11

A report of "Susceptible" indicates that the antimicrobial is likely to inhibit growth of the pathogen if the antibacterial compound in the blood reaches the concentrations usually achievable. A report of "Intermediate" indicates that the result should be considered equivocal, and, if the microorganism is not fully susceptible to alternative, clinically feasible drugs, the test should be repeated. This category implies possible clinical applicability in body sites where the drug is physiologically concentrated or in situations where high dosage of drug can be used. This category also provides a buffer zone that prevents small uncontrolled technical factors from causing major discrepancies in interpretation. A report of "Resistant" indicates that the antimicrobial is not likely to inhibit growth of the pathogen if the antimicrobial compound in the blood reaches the concentrations usually achievable; other therapy should be selected.

Quality control

Standardized susceptibility test procedures require the use of quality control microorganisms to determine the performance of the test procedures^1,2,3. Standard telithromycin powder should provide the MIC ranges for the quality control organisms in Table 4. For the disk diffusion technique, the 15-µg telithromycin disk should provide the zone diameter ranges for the quality control organisms in Table 4.

Table 4. Acceptable Quality Control Ranges for Telithromycin
QC Strain | Minimum Inhibitory Concentrations (µg/mL) | Disk Diffusion (Zone diameter in mm)
Streptococcus pneumoniae ATCC 49619 | 0.004–0.03 | 27–33
Haemophilus influenzae ATCC 49247 | 1.0–4.0 | 17–23
ATCC = American Type Culture Collection

INDICATIONS AND USAGE

KETEK tablets are indicated for the treatment of community-acquired pneumonia (of mild to moderate severity) due to Streptococcus pneumoniae, (including multi-drug resistant isolates [MDRSP [MDRSP, Multi-drug resistant Streptococcus pneumoniae includes isolates known as PRSP (penicillin-resistant Streptococcus pneumoniae), and are isolates resistant to two or more of the following antibiotics: penicillin, 2nd generation cephalosporins, e.g., cefuroxime, macrolides, tetracyclines and trimethoprim/sulfamethoxazole.] ]), Haemophilus influenzae, Moraxella catarrhalis, Chlamydophila pneumoniae, or Mycoplasma pneumoniae, for patients 18 years old and above.

To reduce the development of drug-resistant bacteria and maintain the effectiveness of KETEK and other antibacterial drugs, KETEK should be used only to treat infections that are proven or strongly suspected to be caused by susceptible bacteria. When culture and susceptibility information are available, they should be considered in selecting or modifying antibacterial therapy. In the absence of such data, local epidemiology and susceptibility patterns may contribute to the empiric selection of therapy.

CONTRAINDICATIONS

KETEK is contraindicated in patients with myasthenia gravis. Exacerbations of myasthenia gravis have been reported in patients and sometimes occurred within a few hours of the first dose of telithromycin. Reports have included fatal and life-threatening acute respiratory failure with a rapid onset and progression.

KETEK is contraindicated in patients with previous history of hepatitis and/or jaundice associated with the use of KETEK tablets, or any macrolide antibiotic.

KETEK is contraindicated in patients with a history of hypersensitivity to telithromycin and/or any components of KETEK tablets, or any macrolide antibiotic.

Concomitant administration of KETEK with cisapride or pimozide is contraindicated. (See CLINICAL PHARMACOLOGY, Drug-drug Interactions and PRECAUTIONS.)

Concomitant administration of KETEK and colchicine is contraindicated in patients with renal or hepatic impairment. (See WARNINGS, Drug Interactions and PRECAUTIONS, Drug interactions.)

WARNINGS

Hepatotoxicity

Acute hepatic failure and severe liver injury, in some cases fatal, have been reported in patients treated with KETEK. These hepatic reactions included fulminant hepatitis and hepatic necrosis leading to liver transplant, and were observed during or immediately after treatment. In some of these cases, liver injury progressed rapidly and occurred after administration of a few doses of KETEK. (See ADVERSE REACTIONS)

Physicians and patients should monitor for the appearance of signs or symptoms of hepatitis, such as fatigue, malaise, anorexia, nausea, jaundice, bilirubinuria, acholic stools, liver tenderness or hepatomegaly. Patients with signs or symptoms of hepatitis must be advised to discontinue KETEK and immediately seek medical evaluation, which should include liver function tests. (See ADVERSE REACTIONS, PRECAUTIONS, Information to Patients.) If clinical hepatitis or transaminase elevations combined with other systemic symptoms occur, KETEK should be permanently discontinued.

Ketek must not be re-administered to patients with a previous history of hepatitis and/or jaundice associated with the use of KETEK tablets, or any macrolide antibiotic. (See CONTRAINDICATIONS)

In addition, less severe hepatic dysfunction associated with increased liver enzymes, hepatitis and in some cases jaundice was reported with the use of KETEK. These events associated with less severe forms of liver toxicity were reversible.

QTc prolongation

Telithromycin has the potential to prolong the QTc interval of the electrocardiogram in some patients. QTc prolongation may lead to an increased risk for ventricular arrhythmias, including torsades de pointes. Thus, telithromycin should be avoided in patients with congenital prolongation of the QTc interval, and in patients with ongoing proarrhythmic conditions such as uncorrected hypokalemia or hypomagnesemia, clinically significant bradycardia, and in patients receiving Class IA (e.g., quinidine and procainamide) or Class III (e.g., dofetilide) antiarrhythmic agents.

Cases of torsades de pointes have been reported post-marketing with KETEK. In clinical trials, no cardiovascular morbidity or mortality attributable to QTc prolongation occurred with telithromycin treatment in 4780 patients in clinical trials, including 204 patients having a prolonged QTc at baseline.

Visual disturbances*

KETEK may cause visual disturbances particularly in slowing the ability to accommodate and the ability to release accommodation. Visual disturbances included blurred vision, difficulty focusing, and diplopia. Most events were mild to moderate; however, severe cases have been reported.

Loss of Consciousness*

There have been post-marketing adverse event reports of transient loss of consciousness including some cases associated with vagal syndrome.

*Because of potential visual difficulties or loss of consciousness, patients should attempt to minimize activities such as driving a motor vehicle, operating heavy machinery or engaging in other hazardous activities during treatment with KETEK. If patients experience visual disorders or loss of consciousness while taking KETEK, patients should not drive a motor vehicle, operate heavy machinery or engage in other hazardous activities.
(See PRECAUTIONS, Information for Patients)

Drug Interactions

Serious adverse reactions have been reported in patients taking KETEK concomitantly with CYP 3A4 substrates. These include colchicine toxicity with colchicine; rhabdomyolysis with simvastatin, lovastatin, and atorvastatin; and hypotension with calcium channel blockers metabolized by CYP 3A4 (e.g., verapamil, amlodipine, diltiazem). (See PRECAUTIONS, Drug interactions.)

Life-threatening and fatal drug interactions have been reported in patients treated with colchicine and strong CYP 3A4 inhibitors. Telithromycin is a strong CYP 3A4 inhibitor and this interaction may occur while using both drugs at their recommended doses. If co-administration of telithromycin and colchicine is necessary in patients with normal renal and hepatic function, the dose of colchicine should be reduced. Patients should be monitored for clinical symptoms of colchicine toxicity. Concomitant administration of KETEK and colchicine is contraindicated in patients with renal or hepatic impairment. (See CONTRAINDICATIONS and PRECAUTIONS, Drug interactions.)

Pseudomembranous colitis

Clostridium difficile associated diarrhea (CDAD) has been reported with use of nearly all antibacterial agents, including KETEK, and may range in severity from mild diarrhea to fatal colitis. Treatment with antibacterial agents alters the normal flora of the colon leading to overgrowth of C. difficile.

C. difficile produces toxins A and B which contribute to the development of CDAD. Hypertoxin producing strains of C. difficile cause increased morbidity and mortality, as these infections can be refractory to antimicrobial therapy and may require colectomy. CDAD must be considered in all patients who present with diarrhea following antibiotic use. Careful medical history is necessary since CDAD has been reported to occur over two months after the administration of antibacterial agents.

If CDAD is suspected or confirmed, ongoing antibiotic use not directed against C. difficile may need to be discontinued. Appropriate fluid and electrolyte management, protein supplementation, antibiotic treatment of C difficile, and surgical evaluation should be instituted as clinically indicated.

PRECAUTIONS

General

Prescribing KETEK in the absence of a proven or strongly suspected bacterial infection or a prophylactic indication is unlikely to provide benefit to the patient and increases the risk of the development of drug-resistant bacteria.

Telithromycin is principally excreted via the liver and kidney. Telithromycin may be administered without dosage adjustment in the presence of hepatic impairment. In the presence of severe renal impairment (CLCR < 30 mL/min), a reduced dosage of KETEK is recommended. (See DOSAGE AND ADMINISTRATION)

Information for patients

A Medication Guide is provided to patients when Ketek is dispensed. Patients should be instructed to read the MedGuide when Ketek is received. In addition, the complete text of the MedGuide is reprinted at the end of this document.

The following information and instructions should be communicated to the patient.

- KETEK may cause problems with vision particularly when looking quickly between objects close by and objects far away. These events include blurred vision, difficulty focusing, and objects looking doubled. Most events were mild to moderate; however, severe cases have been reported. Problems with vision were reported as having occurred after any dose during treatment, but most occurred following the first or second dose. These problems lasted several hours and in some patients came back with the next dose. (See WARNINGS and ADVERSE REACTIONS.)

Patients should be advised that avoiding quick changes in viewing between objects in the distance and objects nearby may help to decrease the effects of these visual difficulties.

- Because of potential visual difficulties, loss of consciousness, confusion or hallucinations, patients should attempt to minimize activities such as driving a motor vehicle, operating heavy machinery or engaging in other hazardous activities during treatment with KETEK.

If patients experience visual difficulties, loss of consciousness / fainting, confusion or hallucination

- patients should seek advice from their physician before taking another dose
- patients should not drive a motor vehicle, operate heavy machinery, or engage in otherwise hazardous activities.

Patients should also be advised:

- Ketek is contraindicated in patients with myasthenia gravis.
  (See CONTRAINDICATIONS)
- of the possibility of liver injury, associated with KETEK, which in rare cases may be severe. Patients developing signs or symptoms of liver injury should be instructed to discontinue KETEK and seek medical attention immediately. Symptoms of liver injury may include nausea, fatigue, anorexia, jaundice, dark urine, light-colored stools, pruritus, or tender abdomen. Ketek must not be taken by patients with a previous history of hepatitis/jaundice associated with the use of KETEK or macrolide antibiotics.
  (See CONTRAINDICATIONS and WARNINGS)
- antibacterial drugs including KETEK should only be used to treat bacterial infections. They do not treat viral infections (e.g., the common cold). When KETEK is prescribed to treat a bacterial infection, patients should be told that although it is common to feel better early in the course of therapy, the medication should be taken exactly as directed. Skipping doses or not completing the full course of therapy may (1) decrease the effectiveness of the immediate treatment and (2) increase the likelihood that bacteria will develop resistance and will not be treatable by KETEK or other antibacterial drugs in the future.
- KETEK has the potential to produce changes in the electrocardiogram (QTc interval prolongation) and that they should report any fainting occurring during drug treatment.
- KETEK should be avoided in patients receiving Class 1A (e.g., quinidine, procainamide) or Class III (e.g., dofetilide) antiarrhythmic agents.
- to inform their physician of any personal or family history of QTc prolongation or proarrhythmic conditions such as uncorrected hypokalemia, or clinically significant bradycardia.
- diarrhea is a common problem caused by antibiotics which usually ends when the antibiotic is discontinued. Sometimes after starting treatment with antibiotics, patients can develop watery and bloody stools (with or without stomach cramps and fever) even as late as two or more months after having taken the last dose of the antibiotic. If this occurs, patients should contact their physician as soon as possible.
- simvastatin, lovastatin, or atorvastatin should be avoided in patients receiving KETEK. If KETEK is prescribed, therapy with simvastatin, lovastatin, or atorvastatin should be stopped during the course of treatment. (See CLINICAL PHARMACOLOGY, Drug-drug interactions)
- colchicine should be avoided in patients receiving KETEK. If KETEK is prescribed in patients with normal kidney and liver function, the dose is colchicine should be reduced. Concomitant treatment with KETEK and colchicine is contraindicated in patients with kidney or liver impairment. (See CONTRAINDICATIONS and WARNINGS, Drug interactions.)
- KETEK tablets can be taken with or without food.
- to inform their physician of any other medications taken concurrently with KETEK, including over-the-counter medications and dietary supplements.

Drug interactions

Telithromycin is a strong inhibitor of the cytochrome P450 3A4 system. Co-administration of KETEK tablets and a drug primarily metabolized by the cytochrome P450 3A4 enzyme system may result in increased plasma concentration of the drug co-administered with telithromycin that could increase or prolong both the therapeutic and adverse effects. Therefore, appropriate dosage adjustments may be necessary for the drug co-administered with telithromycin.

The use of KETEK is contraindicated with cisapride. (See CONTRAINDICATIONS and CLINICAL PHARMACOLOGY, Drug-drug interactions)

The use of KETEK is contraindicated with pimozide. Although there are no studies looking at the interaction between KETEK and pimozide, there is a potential risk of increased pimozide plasma levels by inhibition of CYP 3A4 pathways by KETEK as with macrolides. (See CONTRAINDICATIONS)

In a pharmacokinetic study, simvastatin levels were increased due to CYP 3A4 inhibition by telithromycin. (See CLINICAL PHARMACOLOGY, Drug-drug interactions) Similarly, an interaction may occur with lovastatin or atorvastatin but not with statins which are not metabolized by CYP3A4.

High levels of HMG-CoA reductase inhibitors increase the risk of myopathy and rhabdomyolysis. Use of simvastatin, lovastatin, or atorvastatin concomitantly with KETEK should be avoided. If KETEK is prescribed, therapy with simvastatin, lovastatin, or atorvastatin should be suspended during the course of treatment. Patients concomitantly treated with statins should be carefully monitored for signs and symptoms of myopathy and rhabdomyolysis.

Colchicine is a substrate for both CYP 3A4 and the efflux transporter, P-glycoprotein (P-gp), and a significant increase in colchicine plasma concentration is anticipated when co-administered with strong CYP 3A4 inhibitors such as telithromycin. (See CONTRAINDICATIONS and WARNINGS, Drug interactions).

Monitoring of digoxin side effects or serum levels should be considered during concomitant administration of digoxin and KETEK. (See CLINICAL PHARMACOLOGY, Drug-drug interactions.)

Hypotension, bradyarrhythmia and loss of consciousness have been observed in patients receiving concomitant treatment with calcium channel blockers that are substrates of CYP 3A4 (e.g., verapamil, amlodipine, diltiazem).

Patients should be monitored with concomitant administration of midazolam and dosage adjustment of midazolam should be considered if necessary. Precaution should be used with other benzodiazepines, which are metabolized by CYP 3A4 and undergo a high first-pass effect (e.g., triazolam). (See CLINICAL PHARMACOLOGY, Drug-drug interactions.)

Concomitant treatment of KETEK with rifampin, a CYP 3A4 inducer, should be avoided. Concomitant administration of other CYP 3A4 inducers such as phenytoin, carbamazepine, or phenobarbital is likely to result in subtherapeutic levels of telithromycin and loss of effect. (See CLINICAL PHARMACOLOGY, Other drug interactions.)

In patients treated with metoprolol for heart failure, the increased exposure to metoprolol, a CYP 2D6 substrate, may be of clinical importance. Therefore, co-administration of KETEK and metoprolol in patients with heart failure should be considered with caution. (See CLINICAL PHARMACOLOGY, Drug-drug interactions.)

Spontaneous post-marketing reports suggest that administration of KETEK and oral anticoagulants concomitantly may potentiate the effects of the oral anticoagulants. Consideration should be given to monitoring prothrombin times/INR while patients are receiving KETEK and oral anticoagulants simultaneously.

No specific drug interaction studies have been performed to evaluate the following potential drug-drug interactions with KETEK. However, these drug interactions have been observed with macrolide products.

Drugs metabolized by the cytochrome P450 system such as carbamazepine, cyclosporine, tacrolimus, sirolimus, hexobarbital, and phenytoin: elevation of serum levels of these drugs may be observed when co-administered with telithromycin. As a result, increases or prolongation of the therapeutic and/or adverse effects of the concomitant drug may be observed.

Ergot alkaloid derivatives (such as ergotamine or dihydroergotamine): acute ergot toxicity characterized by severe peripheral vasospasm and dysesthesia has been reported when macrolide antibiotics were co-administered. Without further data, the co-administration of KETEK and these drugs is not recommended.

Laboratory test interactions

There are no reported laboratory test interactions.

Carcinogenesis, mutagenesis, impairment of fertility

Long-term studies in animals to determine the carcinogenic potential of KETEK have not been conducted.

Telithromycin showed no evidence of genotoxicity in four tests: gene mutation in bacterial cells, gene mutation in mammalian cells, chromosome aberration in human lymphocytes, and the micronucleus test in the mouse.

No evidence of impaired fertility in the rat was observed at doses estimated to be 0.61 times the human daily dose on a mg/m^2 basis. At doses of 1.8–3.6 times the human daily dose, at which signs of parental toxicity were observed, moderate reductions in fertility indices were noted in male and female animals treated with telithromycin.

Pregnancy

Teratogenic effects

Pregnancy Category C

Telithromycin was not teratogenic in the rat or rabbit. Reproduction studies have been performed in rats and rabbits, with effect on pre-post natal development studied in the rat. At doses estimated to be 1.8 times (900 mg/m^2) and 0.49 times (240 mg/m^2) the daily human dose of 800 mg (492 mg/m^2) in the rat and rabbit, respectively, no evidence of fetal terata was found. At doses higher than the 900 mg/m^2 and 240 mg/m^2 in rats and rabbits, respectively, maternal toxicity may have resulted in delayed fetal maturation. No adverse effects on prenatal and postnatal development of rat pups were observed at 1.5 times (750 mg/m^2/d) the daily human dose.

There are no adequate and well-controlled studies in pregnant women. Telithromycin should be used during pregnancy only if the potential benefit justifies the potential risk to the fetus.

Nursing mothers

Telithromycin is excreted in breast milk of rats. Telithromycin may also be excreted in human milk. Because many drugs are excreted in human milk, caution should be exercised when KETEK is administered to a nursing mother.

Pediatric use

The safety and effectiveness of KETEK in pediatric patients has not been established.

Geriatric use

In all Phase III clinical trials (n=4,780), KETEK was administered to 694 patients who were 65 years and older, including 231 patients who were 75 years and older. Efficacy and safety in elderly patients ≥ 65 years were generally similar to that observed in younger patients; however, greater sensitivity of some older individuals cannot be ruled out. No dosage adjustment is required based on age alone. (See CLINICAL PHARMACOLOGY, Special populations, Geriatric and DOSAGE AND ADMINISTRATION.)

ADVERSE REACTIONS

In Phase III clinical trials, 4,780 patients (n=2702 in controlled trials) received daily oral doses of KETEK 800 mg once daily for 5 days or 7 to 10 days. Most adverse events were mild to moderate in severity. In the combined Phase III studies, discontinuation due to treatment-emergent adverse events occurred in 4.4% of KETEK-treated patients and 4.3% of combined comparator-treated patients. Most discontinuations in the KETEK group were due to treatment-emergent adverse events in the gastrointestinal body system, primarily diarrhea (0.9% for KETEK vs. 0.7% for comparators), nausea (0.7% for KETEK vs. 0.5% for comparators).

All and possibly related treatment-emergent adverse events (TEAEs) occurring in controlled clinical studies in ≥ 2.0% of all patients are included below:

Table 5
All and Possibly Related Treatment-Emergent Adverse Events Reported in Controlled Phase III Clinical Studies (Percent Incidence)
Adverse Event | All TEAEs |  | Possibly-Related TEAEs
 | KETEK n= 2702 | Comparator [Includes comparators from all controlled Phase III studies.] n= 2139 | KETEK n= 2702 | Comparator n= 2139
Diarrhea | 10.8% | 8.6% | 10.0% | 8.0%
Nausea | 7.9% | 4.6% | 7.0% | 4.1%
Headache | 5.5% | 5.8% | 2.0% | 2.5%
Dizziness (excl. vertigo) | 3.7% | 2.7% | 2.8% | 1.5%
Vomiting | 2.9% | 2.2% | 2.4% | 1.4%
Loose Stools | 2.3% | 1.5% | 2.1% | 1.4%
Dysgeusia | 1.6% | 3.6% | 1.5% | 3.6%

The following events judged by investigators to be at least possibly drug related were observed infrequently (≥ 0.2% and < 2%), in KETEK-treated patients in the controlled Phase III studies.

Gastrointestinal system: abdominal distension, dyspepsia, gastrointestinal upset, flatulence, constipation, gastroenteritis, gastritis, anorexia, oral candidiasis, glossitis, stomatitis, watery stools.

Liver and biliary system: abnormal liver function tests: increased transaminases, increased liver enzymes (e.g., ALT, AST) were usually asymptomatic and reversible. ALT elevations above 3 times the upper limit of normal were observed in 1.6%, and 1.7% of patients treated with KETEK and comparators, respectively. Hepatitis, with or without jaundice, occurred in 0.07% of patients treated with KETEK, and was reversible. (See PRECAUTIONS, General.)

Nervous system: dry mouth, somnolence, insomnia, vertigo, increased sweating

Body as a whole: abdominal pain, upper abdominal pain, fatigue

Special senses: Visual adverse events most often included blurred vision, diplopia, or difficulty focusing. Most events were mild to moderate; however, severe cases have been reported. Some patients discontinued therapy due to these adverse events. Visual adverse events were reported as having occurred after any dose during treatment, but most visual adverse events (65%) occurred following the first or second dose. Visual events lasted several hours and recurred upon subsequent dosing in some patients. For patients who continued treatment, some resolved on therapy while others continued to have symptoms until they completed the full course of treatment. (See WARNINGS and PRECAUTIONS, Information for patients.)

Females and patients under 40 years old experienced a higher incidence of telithromycin-associated visual adverse events. (See CLINICAL STUDIES.)

Urogenital system: vaginal candidiasis, vaginitis, vaginosis fungal

Skin: rash

Hematologic: increased platelet count

Other possibly related clinically-relevant events occurring in <0.2% of patients treated with KETEK from the controlled Phase III studies included: anxiety, bradycardia, eczema, elevated blood bilirubin, erythema multiforme, flushing, hypotension, increased blood alkaline phosphatase, increased eosinophil count, paresthesia, pruritus, urticaria.

Post-Marketing Adverse Event Reports

In addition to adverse events reported from clinical trials, the following events have been reported from worldwide post-marketing experience with KETEK.

Allergic: face edema, rare reports of severe allergic (hypersensitivity) reactions, including angioedema and anaphylaxis

Cardiovascular: atrial arrhythmias, palpitations

Gastrointestinal system: pancreatitis

Liver and biliary system: Hepatic dysfunction has been reported.

Severe and in some cases fatal hepatotoxicity, including fulminant hepatitis, hepatic necrosis and hepatic failure have been reported in patients treated with KETEK. These hepatic reactions were observed during or immediately after treatment. In some of these cases, liver injury progressed rapidly and occurred after administration of only a few doses of KETEK. (See CONTRAINDICATIONS and WARNINGS.) Severe reactions, in some but not all cases, have been associated with serious underlying diseases or concomitant medications.

Data from post-marketing reports and clinical trials show that most cases of hepatic dysfunction were mild to moderate. (See PRECAUTIONS, General.)

Musculoskeletal: muscle cramps, rare reports of exacerbation of myasthenia gravis. (See CONTRAINDICATIONS.) arthralgia, myalgia

Nervous system: loss of consciousness, in some cases associated with vagal syndrome.

Psychiatric disorders: confusion, hallucinations (mostly visual)

Special senses: taste/smell perversion and/or loss

OVERDOSAGE

In the event of acute overdosage, the stomach should be emptied by gastric lavage. The patient should be carefully monitored (e.g., ECG, electrolytes) and given symptomatic and supportive treatment. Adequate hydration should be maintained. The effectiveness of hemodialysis in an overdose situation with KETEK is unknown.

DOSAGE AND ADMINISTRATION

The dose of KETEK tablets is 800 mg (2 tablets of 400 mg) taken orally once every 24 hours, for 7–10 days. KETEK tablets can be administered with or without food.

KETEK may be administered without dosage adjustment in the presence of hepatic impairment.

In the presence of severe renal impairment (CLCR < 30 mL/min), including patients who need dialysis, the dose should be reduced to KETEK 600 mg once daily. In patients undergoing hemodialysis, KETEK should be given after the dialysis session on dialysis days. (See CLINICAL PHARMACOLOGY, Renal insufficiency.)

In the presence of severe renal impairment (CLCR < 30 mL/min), with coexisting hepatic impairment, the dose should be reduced to KETEK 400 mg once daily. (See CLINICAL PHARMACOLOGY, Multiple insufficiency.)

HOW SUPPLIED

KETEK® 400 mg tablets are supplied as light-orange, oval, film-coated tablets, imprinted "H3647" on one side and "400" on the other side. These are packaged in bottles or blister cards (Ketek Pak™ and unit dose) as follows:

Ketek Pak™, 10-tablet cards (2 tablets per blister cavity) (NDC 54868-5171-0)

STORAGE AND HANDLING

Store at 25°C (77°F); excursions permitted to 15–30°C (59–86°F) [see USP Controlled Room Temperature].

CLINICAL STUDIES

Community-acquired pneumonia (CAP)

KETEK was studied in four randomized, double-blind, controlled studies and four open-label studies for the treatment of community-acquired pneumonia. Patients with mild to moderate CAP who were considered appropriate for oral outpatient treatment were enrolled in these trials. Patients with severe pneumonia were excluded based on any one of the following: ICU admission, need for parenteral antibiotics, respiratory rate > 30/minute, hypotension, altered mental status, < 90% oxygen saturation by pulse oximetry, or white blood cell count < 4000/mm^3. Total number of clinically evaluable patients in the telithromycin group included 2016 patients.

Table 6. CAP: Clinical cure rate at post-therapy follow-up (17–24 days)
 | Patients (n) |  | Clinical cure rate
Controlled Studies | KETEK | Comparator | KETEK | Comparator
KETEK vs. clarithromycin 500 mg BID for 10 days | 162 | 156 | 88.3% | 88.5%
KETEK vs. trovafloxacin [This study was stopped prematurely after trovafloxacin was restricted for use in hospitalized patients with severe infection.] 200 mg QD for 7 to 10 days | 80 | 86 | 90.0% | 94.2%
KETEK vs. amoxicillin 1000 mg TID for 10 days | 149 | 152 | 94.6% | 90.1%
KETEK for 7 days vs. clarithromycin 500 mg BID for 10 days | 161 | 146 | 88.8% | 91.8%

Clinical cure rates by pathogen from the four CAP controlled clinical trials in microbiologically evaluable patients given KETEK for 7–10 days or a comparator are displayed in Table 7.

Table 7. CAP: Clinical cure rate by pathogen at post-therapy follow-up (17–24 days)
Pathogen | KETEK | Comparator
Streptococcus pneumoniae | 73/78 (93.6%) | 63/70 (90.0%)
Haemophilus influenzae | 39/47 (83.0%) | 42/44 (95.5%)
Moraxella catarrhalis | 12/14 (85.7%) | 7/9 (77.8%)
Chlamydophila (Chlamydia) pneumoniae | 23/25 (92.0%) | 18/19 (94.7%)
Mycoplasma pneumoniae | 22/23 (95.7%) | 20/22 (90.9%)

Clinical cure rates for patients with CAP due to Streptococcus pneumoniae were determined from patients in controlled and uncontrolled trials. Of 333 evaluable patients with CAP due to Streptococcus pneumoniae, 312 (93.7%) achieved clinical success. Only patients considered appropriate for oral outpatient therapy were included in these trials. More severely ill patients were not enrolled. Blood cultures were obtained in all patients participating in the clinical trials of mild to moderate community-acquired pneumonia. In a limited number of outpatients with incidental pneumococcal bacteremia treated with KETEK, a clinical cure rate of 88% (67/76) has been observed. KETEK is not indicated for the treatment of severe community-acquired pneumonia or suspected pneumococcal bacteremia.

Clinical cure rates for patients with CAP due to multi-drug resistant Streptococcus pneumoniae (MDRSP*) were determined from patients in controlled and uncontrolled trials. Of 36 evaluable patients with CAP due to MDRSP, 33 (91.7%) achieved clinical success.

*MDRSP: Multi-drug resistant Streptococcus pneumoniae includes isolates known as PRSP (penicillin-resistant Streptococcus pneumoniae), and are isolates resistant to two or more of the following antibiotics: penicillin, 2nd generation cephalosporins, e.g., cefuroxime, macrolides, tetracyclines and trimethoprim/sulfamethoxazole.

Table 8. Clinical cure rate for 36 evaluable patients with MDRSP treated with KETEK in studies of community-acquired pneumonia
Screening Susceptibility | Clinical Success in Evaluable MDRSP Patients
 | n/N [n = the number of patients successfully treated; N = the number with resistance to the listed drug of the 36 evaluable patients with CAP due to MDRSP.] | %
Penicillin-resistant | 20/23 | 86.9
2nd generation cephalosporin-resistant | 20/22 | 90.9
Macrolide-resistant | 25/28 | 89.3
Trimethoprim/sulfamethoxazole-resistant | 24/27 | 88.9
Tetracycline-resistant [Includes isolates tested for resistance to either tetracycline or doxycycline.] | 11/13 | 84.6

Visual Adverse Events

Table 9 provides the incidence of all treatment-emergent visual adverse events in controlled Phase III studies by age and gender. The group with the highest incidence was females under the age of 40, while males over the age of 40 had rates of visual adverse events similar to comparator-treated patients.

Table 9. Incidence of All Treatment-Emergent Visual Adverse Events in Controlled Phase III Studies
Gender/Age | Telithromycin | Comparators [Includes all comparators combined]
Female ≤ 40 | 2.1% (14/682) | 0.0% (0/534)
Female > 40 | 1.0% (7/703) | 0.35% (2/574)
Male ≤ 40 | 1.2% (7/563) | 0.48% (2/417)
Male > 40 | 0.27% (2/754) | 0.33% (2/614)
Total | 1.1% (30/2702) | 0.28% (6/2139)

ANIMAL PHARMACOLOGY

Repeated dose toxicity studies of 1, 3, and 6 months' duration with telithromycin conducted in rat, dog and monkey showed that the liver was the principal target for toxicity with elevations of liver enzymes and histological evidence of damage. There was evidence of reversibility after cessation of treatment. Plasma exposures based on free fraction of drug at the no observed adverse effect levels ranged from 1 to 10 times the expected clinical exposure.

Phospholipidosis (intracellular phospholipid accumulation) affecting a number of organs and tissues (e.g., liver, kidney, lung, thymus, spleen, gall bladder, mesenteric lymph nodes, GI-tract) has been observed with the administration of telithromycin in rats at repeated doses of 900 mg/m^2/day (1.8× the human dose) or more for 1 month, and 300 mg/m^2/day (0.61× the human dose) or more for 3–6 months. Similarly, phospholipidosis has been observed in dogs with telithromycin at repeated doses of 3000 mg/m^2/day (6.1× the human dose) or more for 1 month and 1000 mg/m^2/day (2.0× the human dose) or more for 3 months. The significance of these findings for humans is unknown.

Pharmacology/toxicology studies showed an effect both in prolonging QTc interval in dogs in vivo and in vitro action potential duration (APD) in rabbit Purkinje fibers. These effects were observed at concentrations of free drug at least 8.8 (in dogs) times those circulating in clinical use. In vitro electrophysiological studies (hERG assays) suggested an inhibition of the rapid activating component of the delayed rectifier potassium current (IKr) as an underlying mechanism.

Revised December 2010

sanofi-aventis U.S. LLC
Bridgewater, NJ 08807
© 2010 sanofi-aventis U.S. LLC

Additional barcode labeling by:
Physicians Total Care, Inc.
Tulsa, Oklahoma 74146

REFERENCES

1. National Committee for Clinical Laboratory Standards. Methods for Dilution Antimicrobial Susceptibility Tests for Bacteria That Grow Aerobically – Sixth Edition; Approved Standard, NCCLS Document M7-A6, Vol. 23, No. 2, NCCLS, Wayne, PA, January, 2003.
2. National Committee for Clinical Laboratory Standards. Performance Standards for Antimicrobial Disk Susceptibility Tests - Eighth Edition; Approved Standard, NCCLS Document M2-A8, Vol. 23, No. 1, NCCLS, Wayne, PA, January, 2003.
3. National Committee for Clinical Laboratory Standards. Performance Standards for Antimicrobial Susceptibility Testing: Twelfth Informational Supplement; Approved Standard, NCCLS Document M2-A8 and M7-A6, Vol. 23, No. 1, NCCLS, Wayne, PA, January, 2004.

Medication Guide

KETEK® (KEE tek)
(telithromycin)
Tablets

Read the Medication Guide that comes with KETEK before you start taking it and each time you get a new prescription. There may be new information. Talk to your doctor if you have any questions about KETEK. This Medication Guide does not take the place of talking with your doctor about your medical condition or treatment.

What is the most important information I should know about KETEK?

Do not take KETEK if you have myasthenia gravis (a rare disease which causes muscle weakness). Worsening of myasthenia gravis symptoms including life-threatening breathing problems have happened in people with myasthenia gravis after taking KETEK, in some cases leading to death.

KETEK can cause other serious side effects, including:

1. Severe liver damage (hepatotoxicity). Severe liver damage, in some cases leading to a liver transplant or death has happened in people treated with KETEK. Severe liver damage has happened during treatment, even after a few doses, or right after treatment with KETEK has ended.

Stop taking KETEK and call your doctor right away if you have signs of liver problems. Do not take another dose of KETEK unless your doctor tells you to.

Signs of liver problems include:

- increased tiredness
- loss of appetite
- nausea
- yellowing of your skin or whites of your eyes

- dark colored urine (tea colored)
- light colored stools
- right upper belly pain
- itchy skin

Do not take KETEK if you have ever had liver problems while taking KETEK or macrolide antibiotics. Macrolide antibiotics include:

- erythromycin
- azithromycin (Zithromax®, Zmax®)
- clarithromycin (Biaxin®)
- dirithromycin (Dynabac®)

2. Vision problems. KETEK may cause you to have blurred vision, trouble focusing your eyes, and double vision. You may especially notice vision problems if you look quickly between objects close to you and objects far away from you.
3. Fainting. KETEK may cause you to faint, especially if you also have nausea, vomiting, and lightheadedness.

Do not drive, operate heavy machinery, or do other dangerous activities while taking KETEK if you have:

- vision problems
- fainting
- confusion
- seeing things that are not there (visual hallucinations)

Stop taking KETEK and call your doctor right away if you have any of these symptoms. Do not take another dose of KETEK unless your doctor tells you to.

4. Low blood pressure, slow heart rate, and fainting. Ketek may cause you to have low blood pressure, a slow heart rate, and fainting when you also take certain medicines called calcium channel blockers. Calcium channel blockers include:

- verapamil (Calan®)
- amlodipine (Norvasc®)
- diltiazem (Cardizem®)
- or other medications containing these products.

See "What are the possible side effects of KETEK?"

What is KETEK?

KETEK is an antibiotic. KETEK is used to treat adults 18 years of age and older with a lung infection called "community acquired pneumonia" that is caused by certain germs called bacteria.

- KETEK is not for other types of infections.
- KETEK does not kill viruses like the common cold.

Who should not take KETEK?

Do not take KETEK if you:

- have myasthenia gravis
- have had liver problems while taking KETEK or macrolide antibiotics.
- have ever had an allergic reaction to telithromycin in KETEK or macrolide antibiotics.
- take cisapride (Propulsid®) or pimozide (Orap®).
- take colchicine (Colcrys®) and have kidney or liver problems.

Talk to your doctor before taking KETEK if you have any of the conditions listed above.

What should I tell my doctor before taking KETEK?

Before taking KETEK, tell your doctor if you:

- have liver problems
- have a heart problem called "QTc prolongation" or have a family history of QTc prolongation
- have other heart problems
- are pregnant or plan to become pregnant. It is not known if KETEK will harm your unborn baby. Talk to your doctor if you are pregnant or plan to become pregnant.
- are breast-feeding or plan to breast-feed. It is not known if KETEK passes into your breast milk. Talk to your doctor about the best way to feed your baby if you take KETEK.

Tell your doctor about all of the medicines you take, including prescription and nonprescription medicines, vitamins, and herbal supplements. KETEK and other medicines may affect or interact with each other, sometimes causing serious side effects.

Especially tell your doctor if you take:

- colchicine (Colcrys®) while you take KETEK
- certain medicines called calcium channel blockers, such as: verapamil (Calan®), amlodipine (Norvasc®), diltiazem (Cardizem®), or other medications containing these products while you take KETEK
- cholesterol lowering medicines; you should not take these cholesterol lowering medicines while taking KETEK:
  - simvastatin (Zocor®, Vytorin®)
  - lovastatin (Mevacor®)
  - atorvastatin (Lipitor®)

Ask your doctor if you are not sure if the medicine you take is included in the list of medicines above.

Know the medicines you take. Keep a list of your medicines with you to show your doctor or pharmacist.

Do not take other medicines with KETEK without first checking with your doctor. Your doctor will tell you if you can take other medicines while taking KETEK.

How should I take KETEK?

- Take KETEK exactly as your doctor tells you.
- Skipping doses or not taking all of an antibiotic may:
  - make the treatment not work as well
  - increase the chance that the bacteria will develop resistance to the antibiotic
- If you have kidney disease, your doctor may prescribe a lower dose for you.
- Take KETEK with or without food.
- Swallow KETEK tablets whole.
- If you take too much KETEK, call your doctor, or go to the nearest hospital emergency room right away.

What are the possible side effects of KETEK?

See "What is the most important information I should know about KETEK?"

KETEK may cause serious side effects, including:

- Pseudomembranous colitis (an intestine infection). Pseudomembranous colitis can happen with most antibiotics, including KETEK. Call your doctor if you get watery diarrhea, diarrhea that does not go away, or bloody stools. You may also have stomach cramps and a fever. Pseudomembranous colitis can happen up to 2 months after you have finished your antibiotic.

The most common side effects of KETEK are:

- nausea
- headache
- dizziness
- vomiting
- diarrhea
- problems with taste

Tell your doctor if you have any side effect that bothers you or that does not go away.

These are not all of the possible side effects of KETEK. For more information ask your doctor or pharmacist.

Call your doctor for medical advice about side effects. You may report side effects to FDA at 1-800-FDA-1088.

You may also report side effects to sanofi-aventis U.S. at 1-800-633-1610.

How should I store KETEK?

- Store KETEK tablets at room temperature, between 59°F to 86°F (15°C to 30°C).
- Keep KETEK and all medicines out of the reach of children.

General Information about KETEK

- Medicines are sometimes prescribed for purposes other than those listed in a Medication Guide. Do not use KETEK for a condition for which it was not prescribed. Do not share KETEK with other people, even if they have the same symptoms that you have. It may harm them.

This Medication Guide summarizes the most important information about KETEK. If you would like more information, talk with your doctor. You can ask your doctor or pharmacist for information about KETEK that was written for healthcare professionals. This information is also available on the KETEK website at www.KETEK.com or call 1-800-446-6267.

What are the ingredients in KETEK?

Active Ingredient: telithromycin

Inactive Ingredients: croscarmellose sodium, hypromellose, magnesium stearate, microcrystalline cellulose, polyethylene glycol, povidone, red ferric oxide, talc, titanium dioxide, and yellow ferric oxide

Revised December 2010

This Medication Guide has been approved by the U.S. Food and Drug Administration.

sanofi-aventis U.S. LLC
Bridgewater, NJ 08807

© 2010 sanofi-aventis U.S. LLC

BIAXIN® (clarithromycin) is a registered trademark of Abbott Laboratories.
ZITHROMAX® (azithromycin) is a registered trademark of Pfizer Inc.
DYNABAC® (dirithromycin) is a registered trademark of Eli Lilly and Company.
PROPULSID® (cisapride) is a registered trademark of Johnson & Johnson.
ORAP® (pimozide) is a registered trademark of Teva Pharmaceuticals USA, Inc.
LIPITOR® (atorvastatin) is a registered trademark of Pfizer Inc.
ZOCOR® (simvastatin) is a registered trademark of Merck & Co Inc.
VYTORIN® (simvastatin and ezetimibe) is a registered trademark of Merck/Schering Plough Pharmaceuticals.
MEVACOR® (lovastatin) is a registered trademark of Merck & Co Inc.

PRINCIPAL DISPLAY PANEL - 400 mg Tablets

NDC 54868-5171-0

Ketek®
TELITHROMYCIN
400mg

Dispense with attached Medication Guide

10-Tablets Ketek Pak™